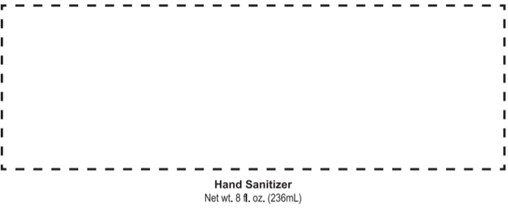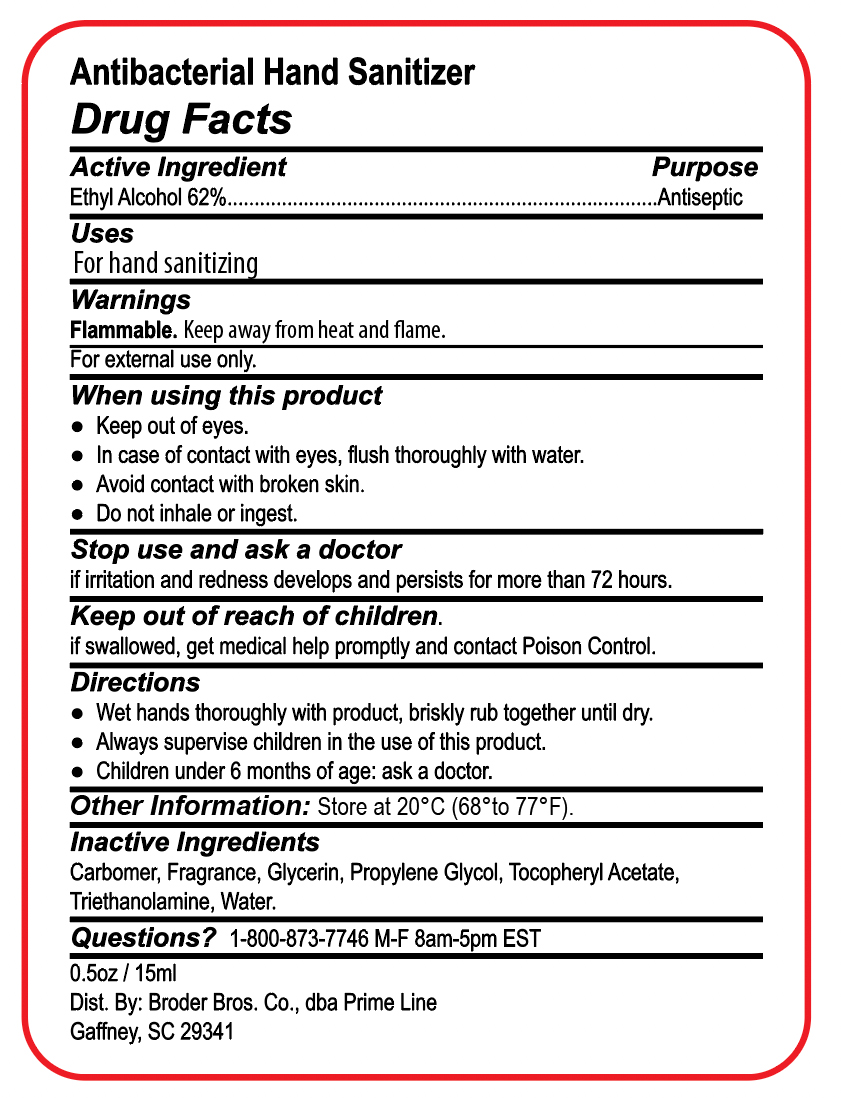 DRUG LABEL: Antibacterial Hand Sanitizer
NDC: 71513-105 | Form: GEL
Manufacturer: Broder Bros Co.
Category: otc | Type: HUMAN OTC DRUG LABEL
Date: 20251117

ACTIVE INGREDIENTS: ALCOHOL 62 mL/100 mL
INACTIVE INGREDIENTS: WATER; TROLAMINE; GLYCERIN; PROPYLENE GLYCOL; .ALPHA.-TOCOPHEROL ACETATE; CARBOXYPOLYMETHYLENE

Antibacterial Hand Sanitizer PC184, PC170, PC192, PC193, PC199, PC188

Active Ingredient

Ethyl Alcohol 62%

Purpose

Antiseptic

Uses

For hand sanitizing

Warnings

Flammable. Keep away from heat and flame.

For external use only

When using this product

- Keep out of eyes
- In case of contact with eyes, flush thoroughly with water
- Avoid contact with broken skin
- Do not inhale or ingest

Stop use and ask a doctor

if irritation and redness develops and persists for more than 72 hours

Keep out of reach of children

if swallowed, get medical help promptly and contact Poison Control

Directions

- Wet hands thoroughly with product, briskly rub together until dry
- Always supervise children in the use of this product
- Children under 6 months of age: ask a doctor

Other Information

Store at 20° C (68° to 77°F)

Inactive ingredients

Carbomer, fragrance, glycerin, propylene glycol, tocopheryl acetate, triethanolamine, water

Questions?

1-800-873-7746 M-F 8am - 5pm EST

0.5 oz / 15 ml

Dist. By: Broder Bros. Co., dba Prime Line

Gaffney, SC 29341